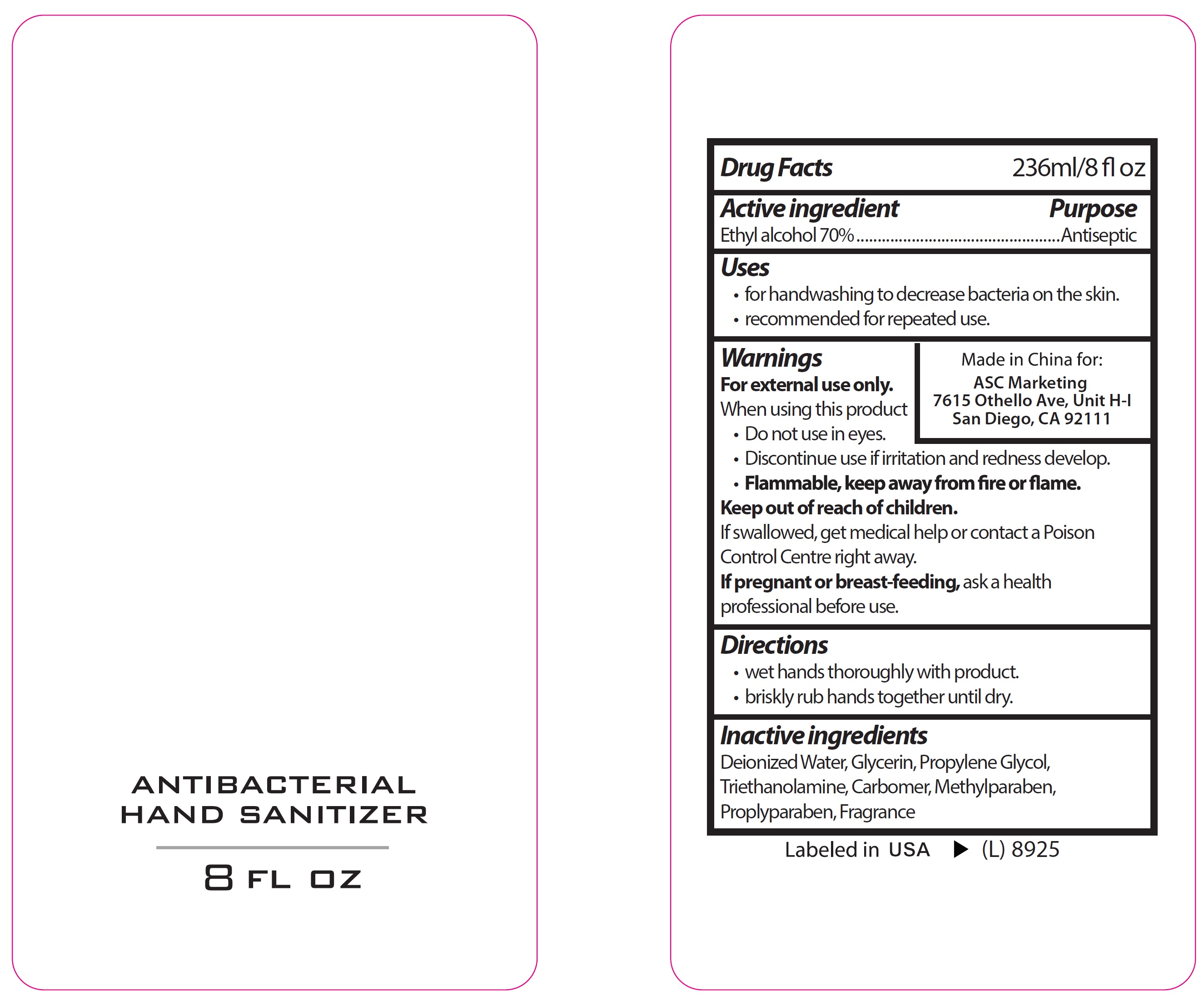 DRUG LABEL: Antibacterial Hand Sanitizer
NDC: 73145-004 | Form: GEL
Manufacturer: ASC Marketing LTD
Category: otc | Type: HUMAN OTC DRUG LABEL
Date: 20231201

ACTIVE INGREDIENTS: ALCOHOL 0.7 mL/1 mL
INACTIVE INGREDIENTS: WATER; GLYCERIN; PROPYLENE GLYCOL; TROLAMINE; CARBOMER HOMOPOLYMER, UNSPECIFIED TYPE; METHYLPARABEN; PROPYLPARABEN

Antibacterial Hand Sanitizer

Active ingredient

Ethyl alcohol 70%

Purpose

Antiseptic

Uses

- for handwashing to decrease bacteria on the skin.
- recommended for repeated use.

Warnings

For external use only.

When using this product

• Do not use in eyes. • Discontinue use if irritation and redness develop.

Flammable, keep away from fire or flame.

Keep out of reach of children.

If swallowed, get medical help or contact a Poison Control Centre right away.

If pregnant or breast-feeding,

ask a health professional before use.

Directions

• wet hands thoroughly with product. • briskly rub hands together until dry.

Inactive ingredients

Deionized Water, Glycerin, Propylene Glycol, Triethanolamine, Carbomer, Methylparaben, Proplyparaben, Fragrance